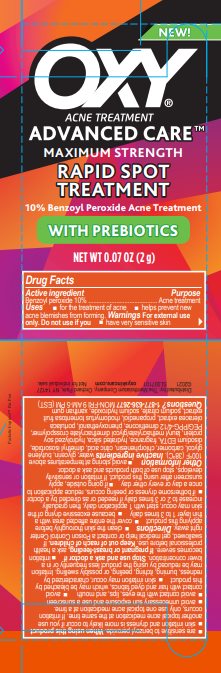 DRUG LABEL: Oxy
NDC: 10742-1205 | Form: GEL
Manufacturer: The Mentholatum Company
Category: otc | Type: HUMAN OTC DRUG LABEL
Date: 20241213

ACTIVE INGREDIENTS: BENZOYL PEROXIDE 100 mg/1 g
INACTIVE INGREDIENTS: WATER; GLYCERIN; BUTYLENE GLYCOL; CARBOMER HOMOPOLYMER TYPE C (ALLYL PENTAERYTHRITOL CROSSLINKED); CHLORPHENESIN; ANHYDROUS CITRIC ACID; DIMETHYL ISOSORBIDE; EDETATE DISODIUM; HYDRATED SILICA; SOY PROTEIN; LAURYL METHACRYLATE/GLYCOL DIMETHACRYLATE CROSSPOLYMER; PEG/PPG-4/12 DIMETHICONE; PHENOXYETHANOL; PURSLANE; PROPANEDIOL; RHODOMYRTUS TOMENTOSA FRUIT; SODIUM CITRATE, UNSPECIFIED FORM; SODIUM HYDROXIDE; XANTHAN GUM

Drug Facts - OXY Advanced Care Rapid Spot Treatment

Active ingredient

Benzoyl peroxide 10%

Purpose

Acne treatment

Uses

- for the treatment of acne
- helps prevent new acne blemishes from forming

Warnings

For external use only

Do not use if you

- have very sensitive skin
- are sensitive to benzoyl peroxide

When using this product

- skin irritation and dryness is more likely to occur if you use another topical acne medication at the same time. If irritation occurs, only use one topical acne medication at a time.
- avoid unnecessary sun exposure and use a sunscreen
- avoid contact with the eyes, lips, and mouth
- avoid contact with hair and dyed fabrics, which may be bleached by this product
- skin irritation may occur, characterized by redness, burning, itching, peeling, or possibly swelling. Irritation may be reduced by using the product less frequently or in a lower concentration.

Stop use and ask a doctor if

- irritation becomes severe

If pregnant or breast-feeding,

ask a health professional before use.

Keep out of reach of children.

If swallowed, get medical help or contact a Poison Control Center right away.

Directions

- clean the skin thoroughly before applying this product
- cover the entire affected area with a thin layer 1 to 3 times daily
- because excessive drying of the skin may occur, start with 1 application daily, then gradually increase to 2 or 3 times daily if needed or as directed by a doctor
- if bothersome dryness or peeling occurs, reduce application to once a day or every other day
- if going outside, apply sunscreen after using this product. If irritation or sensitivity develops, stop use of both products and ask a doctor.

Other Safety Information

- avoid storing at temperatures above 100OF (38OC)

Inactive Ingredients

water, glycerin, butylene glycol, carbomer, chlorphenesin, citric acid, dimethyl isosorbide, disodium EDTA, fragrance, hydrated silica, hydrolyzed soy protein, lauryl methacrylate/glycol dimethacrylate crosspolymer, PEG/PPG-4/12 dimethicone, phenoxyethanol, portulaca oleracea extract, propanediol, rhodomyrtus tomentosa fruit extract, sodium citrate, sodium hydroxide, xanthan gum

Questions

1-877-636-2677 MON-FRI 9 AM-5 PM (EST)